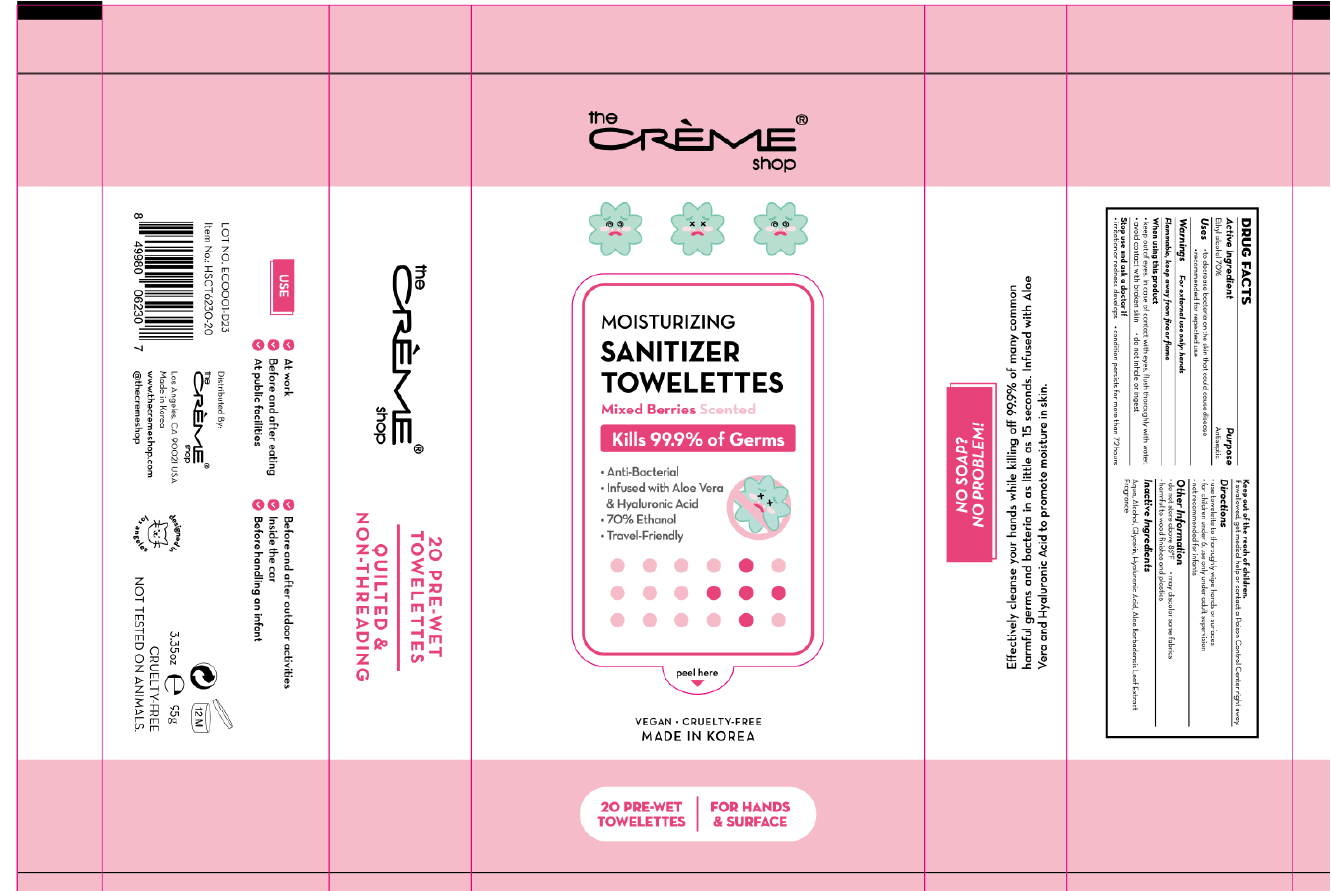 DRUG LABEL: The creme shop Moisturizing Sanitizer Towelettes Mixed Berries Scented
NDC: 74741-7207 | Form: CLOTH
Manufacturer: MPRBRAIN CO.LTD
Category: otc | Type: HUMAN OTC DRUG LABEL
Date: 20200508

ACTIVE INGREDIENTS: ALCOHOL 0.7 g/1 1
INACTIVE INGREDIENTS: ALOE VERA LEAF; GLYCERIN; HYALURONIC ACID; WATER

The creme shop Moisturizing Sanitizer Towelettes Mixed Berries Scented : 20 Towelettes
74741-7207-1